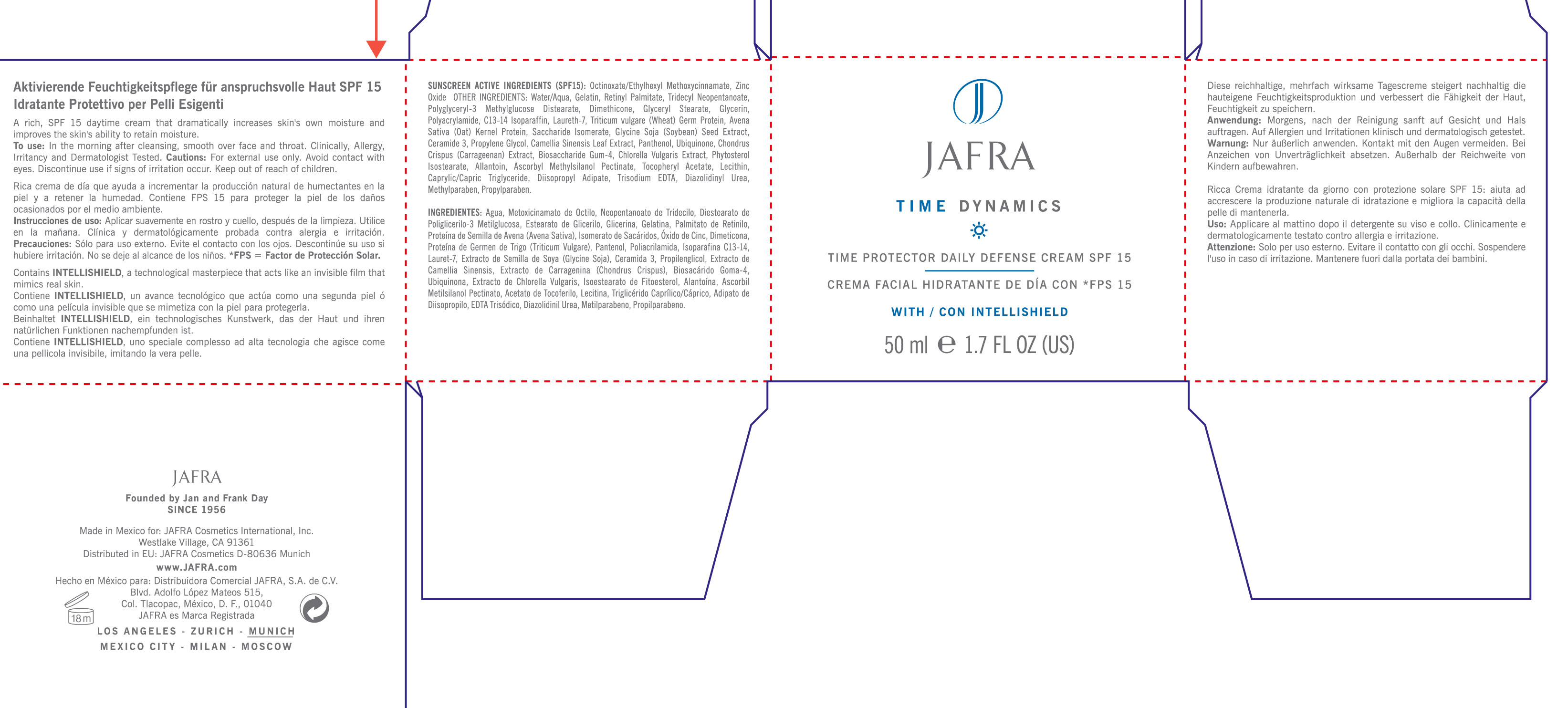 DRUG LABEL: Time Dynamics
NDC: 68828-098 | Form: CREAM, AUGMENTED
Manufacturer: Jafra Cosmetics International Inc
Category: otc | Type: HUMAN OTC DRUG LABEL
Date: 20120613

ACTIVE INGREDIENTS: OCTINOXATE 3.75 mL/50 mL; ZINC OXIDE 1.5 mL/50 mL
INACTIVE INGREDIENTS: WATER; GELATIN; VITAMIN A PALMITATE; TRIDECYL NEOPENTANOATE; DIMETHICONE; GLYCERYL MONOSTEARATE; GLYCERIN; POLYACRYLAMIDE (1500 MW); C13-14 ISOPARAFFIN; LAURETH-7; WHEAT GERM; SACCHARIDE ISOMERATE; SOYBEAN; CERAMIDE 3; PROPYLENE GLYCOL; GREEN TEA LEAF; PANTHENOL; UBIDECARENONE; CHONDRUS CRISPUS; CHLORELLA VULGARIS; ALLANTOIN; ASCORBYL METHYLSILANOL PECTINATE; .ALPHA.-TOCOPHEROL ACETATE; EGG PHOSPHOLIPIDS; MEDIUM-CHAIN TRIGLYCERIDES; DIISOPROPYL ADIPATE; EDETATE TRISODIUM; DIAZOLIDINYL UREA; METHYLPARABEN; PROPYLPARABEN

Time Protector Daily Defense Cream SPF 15

ACTIVE INGREDIENT

Sunscreen Active Ingredients (SPF 15): Octinoxate/Ethylhexyl Methoxycinnamate, Zinc Oxide

Purpose: Sunscreen

Keep out of reach of children

INDICATIONS AND USAGE

Discontinue use if signs of irritation occur.

WARNINGS

Cautions: For external use only. Avoid contact with eyes.

DOSAGE AND ADMINISTRATION

To use: In the morning after cleansing. Smooth over face and throat. Clinically, allergy, irritancy tested.

INACTIVE INGREDIENT

Other ingredients: Water/Aqua, Gelatin, Retinyl Palmitate, Tridecyl Neopentanoate, Polyglyceryl-3 Methylglucose Distearate, Dimethicone, Glyceryl Stearate, Glycerin, Polacrylamide, C13-14 Isoparaffin, Laureth-7, Triticum Vulgare (wheat) Germ Protein, Avena Sativa (Oat) Kernel Protein, Saccharide Isomerate, Glycine Soja (Soybean) Seed Extract, Ceramide 3, Propylene Glycol, Camellia Sinensis Leaf Extract, Panthenol, Ubiquinone, Chondrus Crispus (Carrageenan) Extract, Biosaccharide Gum-4, Chlorella Vulgaris Extract, Phytosterol Isostearate, Allantoin, Ascorbyl Methylsilanol Pectinate, Tocopheryl Acetate, Lecithin, Caprylic/Capric Triglyceride, Diisopropyl Adipate, Trisodium EDTA, Diazolidinyl Urea, Methylparaben, Propylparaben.

PACKAGE LABEL

Jafra
Time Dynamics
Time protector Daily Defense Cream SPF 15
Crema Facial Hidratante De Dia Con *FPS 15
with/con intellishield
50 ml 1.7 Fl Oz